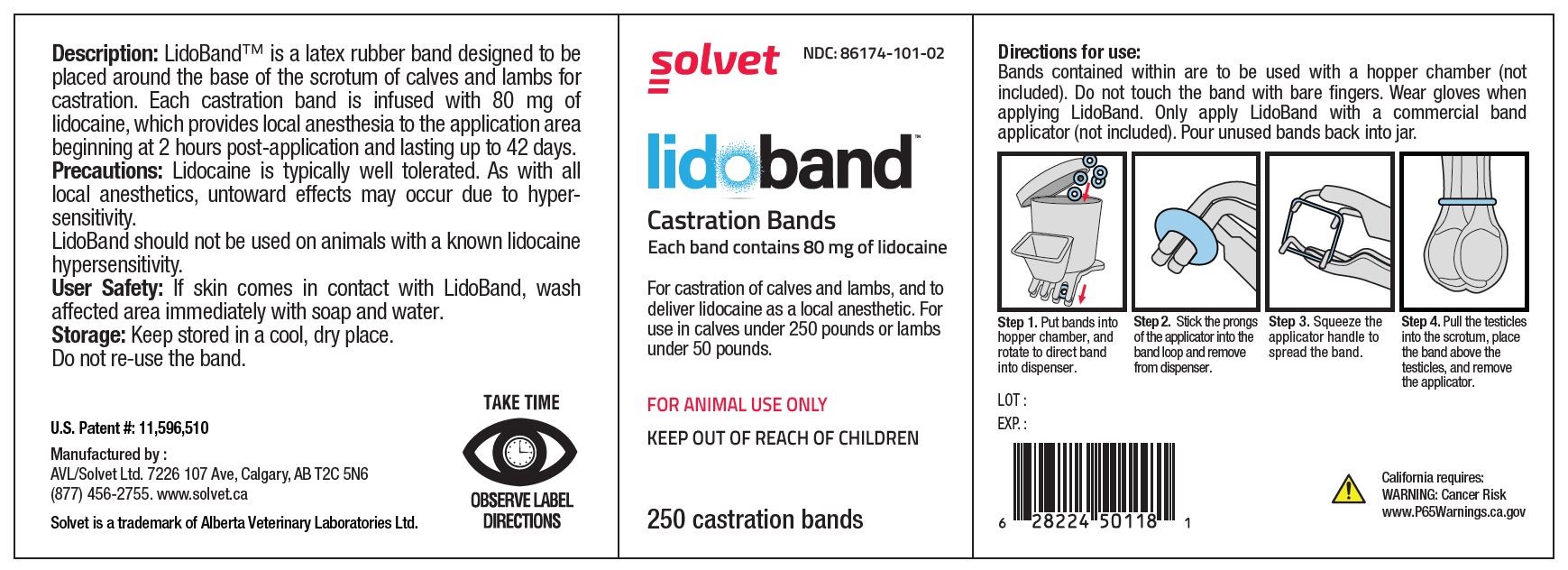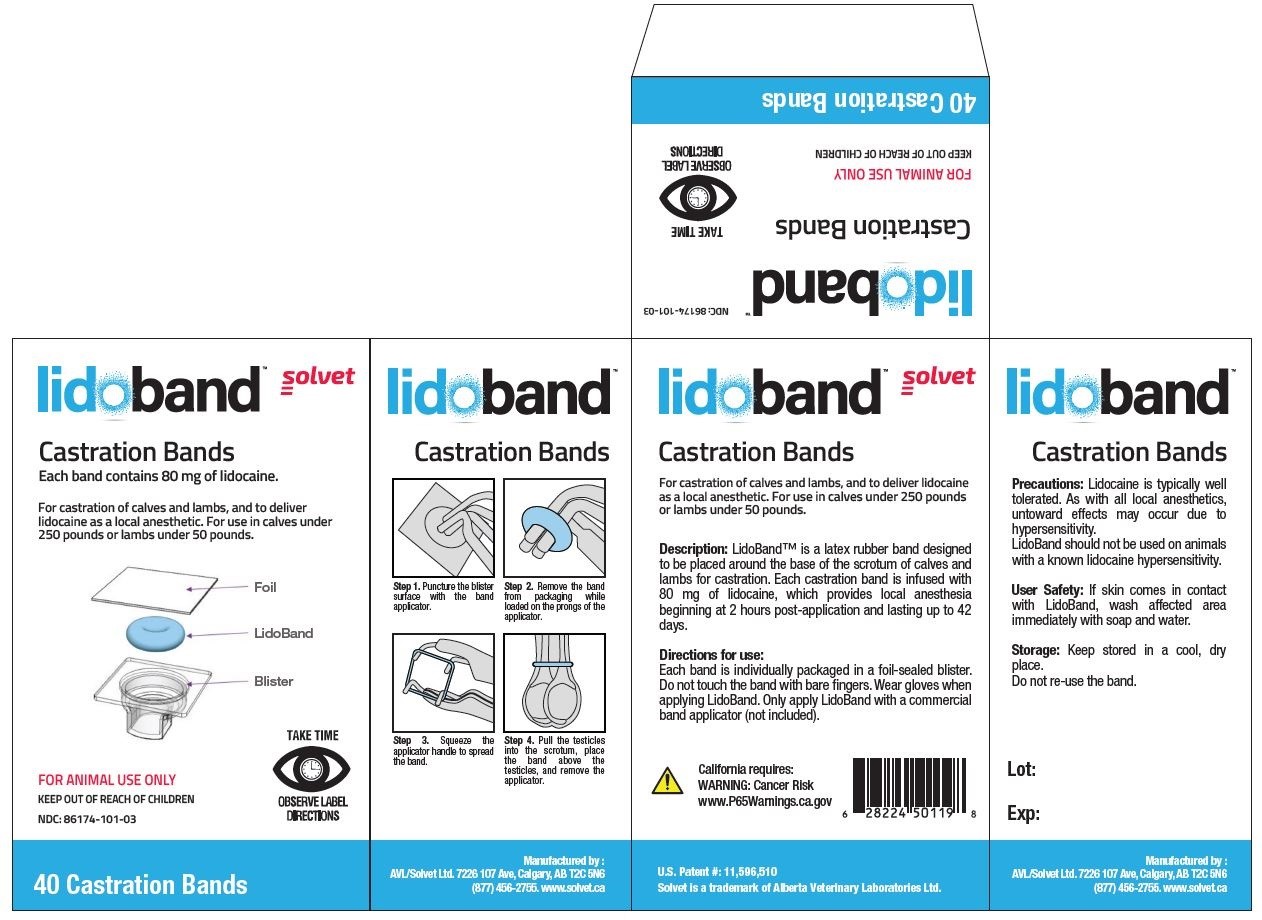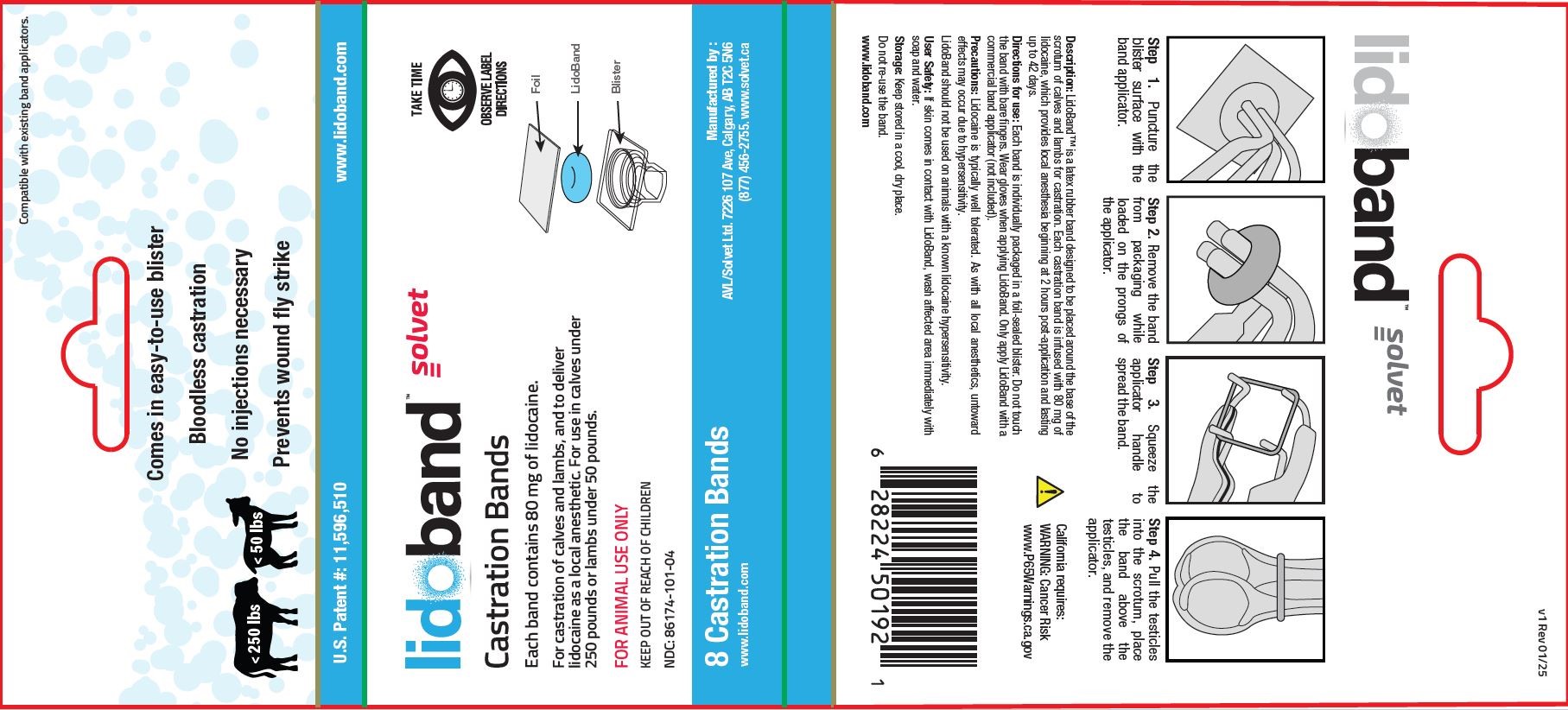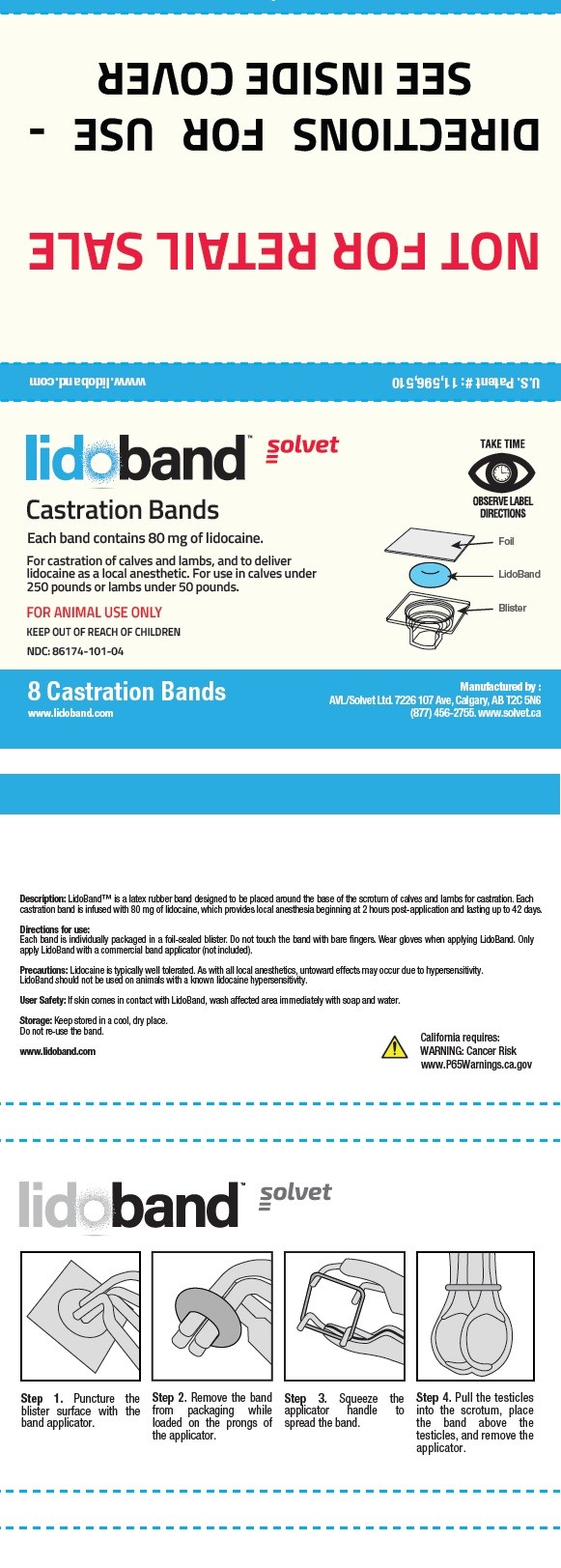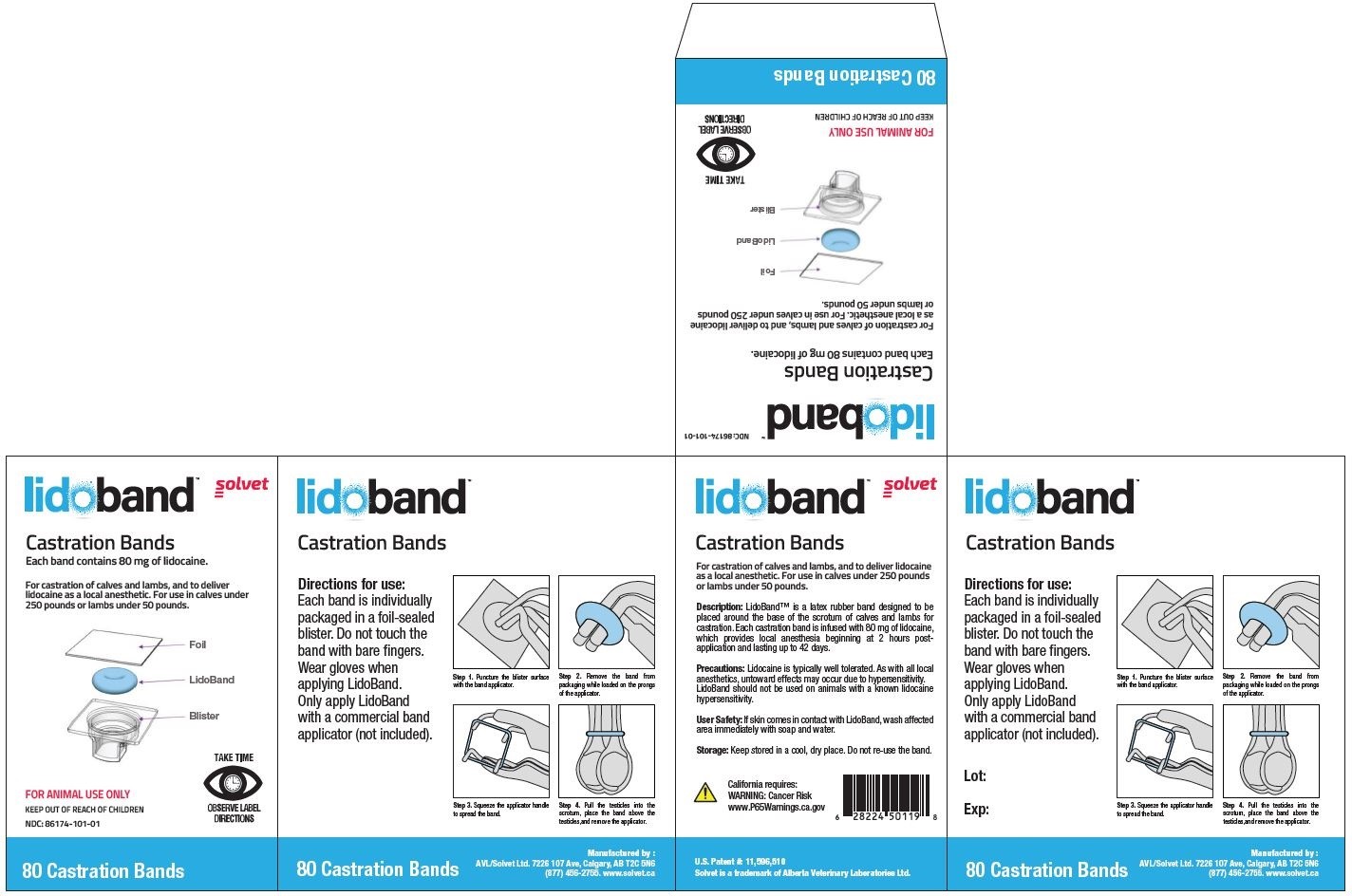 DRUG LABEL: LidoBand
NDC: 86174-101 | Form: RING
Manufacturer: Alberta Veterinary Laboratories Ltd
Category: animal | Type: OTC ANIMAL DRUG LABEL
Date: 20251216

ACTIVE INGREDIENTS: LIDOCAINE 80 mg/1 1
INACTIVE INGREDIENTS: ISOPROPYL MYRISTATE 30 mg/1 1

LidoBand Castration Bands

LidoBand Castration Bands

Solvet

LidoBand Castration Bands

Each band contains 80 mg of lidocaine.

For castration of calves and lambs, and to deliver lidocaine as a local anesthetic. For use in calves under 250 pounds or lambs under 50 pounds.

FOR ANIMAL USE ONLY

KEEP OUT OF REACH OF CHILDREN

TAKE TIME OBSERVE LABEL DIRECTIONS

Description:

LidoBand™ is a latex rubber band designed to be placed around the base of the scrotum of calves and lambs for castration. Each castration band is infused with 80 mg of lidocaine, which provides local anesthesia to the application area beginning at 2 hours post-application and lasting up to 42 days.

Precautions:

Lidocaine is typically well tolerated. As with all local anesthetics, untoward effects may occur due to hypersensitivity.

LidoBand should not be used on animals with a known lidocaine hypersensitivity.

User Safety:

If skin comes in contact with LidoBand, wash affected area immediately with soap and water.

Storage:

Keep stored in a cool, dry place.

Do not re-use the band.

Directions for use: (8, 40, or 80-count box)

Each band is individually packaged in a foil-sealed blister. Do not touch the band with bare fingers. Wear gloves when applying LidoBand. Only apply LidoBand with a commercial band applicator (not included).

Step 1. Puncture the blister surface with the band applicator.

Step 2. Remove the band from packaging while loaded on the prongs of the applicator.

Step 3. Squeeze the applicator handle to spread the band.

Step 4. Pull the testicles into the scrotum, place the band above the testicles, and remove the applicator.

Directions for use: (250 count jar)

Bands contained within are to be used with a hopper chamber (not included). Do not touch the band with bare fingers. Wear gloves when applying LidoBand. Only apply LidoBand with a commercial band applicator (not included). Pour unused bands back into jar.

Step 1. Put bands into hopper chamber, and rotate to direct band into dispenser.

Step 2. Stick the prongs of the applicator into the band loop and remove from dispenser.

Step 3. Squeeze the applicator handle to spread the band.

Step 4. Pull the testicles into the scrotum, place the band above the testicles, and remove the applicator.

Product Label

LidoBand 8 Count Box

LidoBand 8 Count Sample

LidoBand 40 Count Box

LidoBand 80 Count Box

LidoBand 250 Count Jar